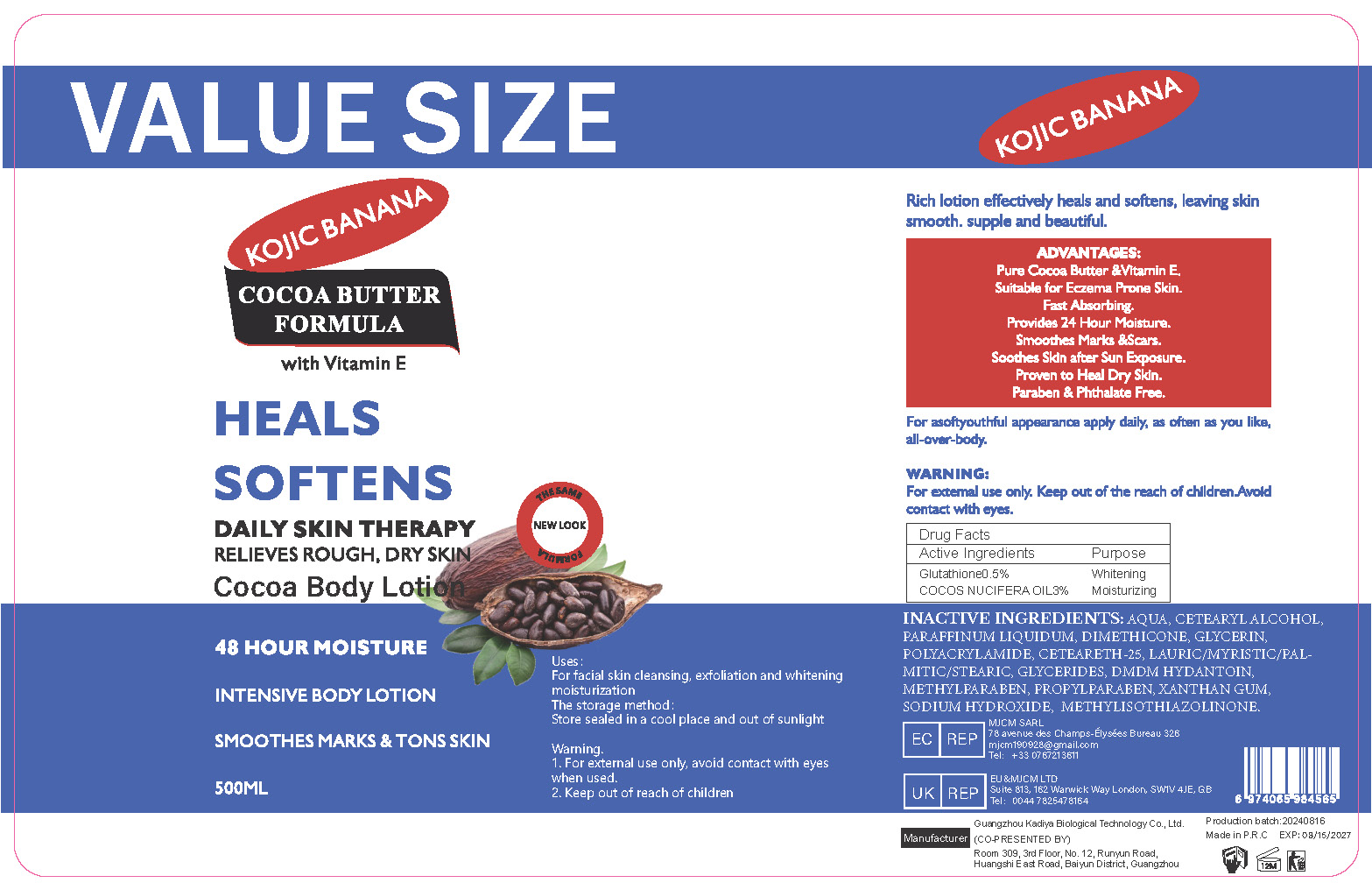 DRUG LABEL: Cocoa BodyLotion
NDC: 84423-043 | Form: EMULSION
Manufacturer: Guangzhou Kadiya Biotechnology Co., Ltd.
Category: otc | Type: HUMAN OTC DRUG LABEL
Date: 20240827

ACTIVE INGREDIENTS: GLUTATHIONE 2.5 mg/500 mL; COCONUT OIL 15 mg/500 mL
INACTIVE INGREDIENTS: GLYCERIN; POLYACRYLAMIDE (10000 MW); WATER; CETOSTEARYL ALCOHOL; CETEARETH-25; DMDM HYDANTOIN; XANTHAN GUM; DIMETHICONE; SODIUM HYDROXIDE; METHYLISOTHIAZOLINONE; MINERAL OIL; METHYLPARABEN; PROPYLPARABEN

PURPOSE

For facial skin cleansing, exfoliation and whitening moisturization

INACTIVE INGREDIENT

AQUA、CETEARYL ALCOHOL、PARAFFINUM LIQUIDUM、DIMETHICONE、GLYCERIN、POLYACRYLAMIDE、CETEARETH-25、LAURIC/MYRISTIC/PALMITIC/STEARIC、GLYCERIDES、DMDM HYDANTOIN、METHYLPARABEN、PROPYLPARABEN、XANTHAN GUM、SODIUM HYDROXIDE、 METHYLISOTHIAZOLINONE

Warning.
1、For external use only, avoid contact with eyes when used
2、Keep out of reach of children

INDICATIONS AND USAGE

Rich lotion effectively heals and softens, leaving skin smooth. supple and beautiful.

DOSAGE AND ADMINISTRATION

For asoftyouthful appearance apply daily, as often as you like, all-over-body

KEEP OUT OF REACH OF CHILDREN SECTION

ACTIVE INGREDIENT

Glutathione0.5%
COCOS NUCIFERA OIL3%

PACKAGE LABEL

Active Ingredients
Glutathione0.5%
COCOS NUCIFERA OIL3%

Uses：
For facial skin cleansing, exfoliation and whitening moisturization
The storage method：
Store sealed in a cool place and out of sunlight

Warning.
1、For external use only, avoid contact with eyes when used
2、Keep out of reach of children

Inactive ingredients：
AQUA、CETEARYL ALCOHOL、PARAFFINUM LIQUIDUM、DIMETHICONE、GLYCERIN、POLYACRYLAMIDE、CETEARETH-25、LAURIC/MYRISTIC/PALMITIC/STEARIC、GLYCERIDES、DMDM HYDANTOIN、METHYLPARABEN、PROPYLPARABEN、XANTHAN GUM、SODIUM HYDROXIDE、 METHYLISOTHIAZOLINONE